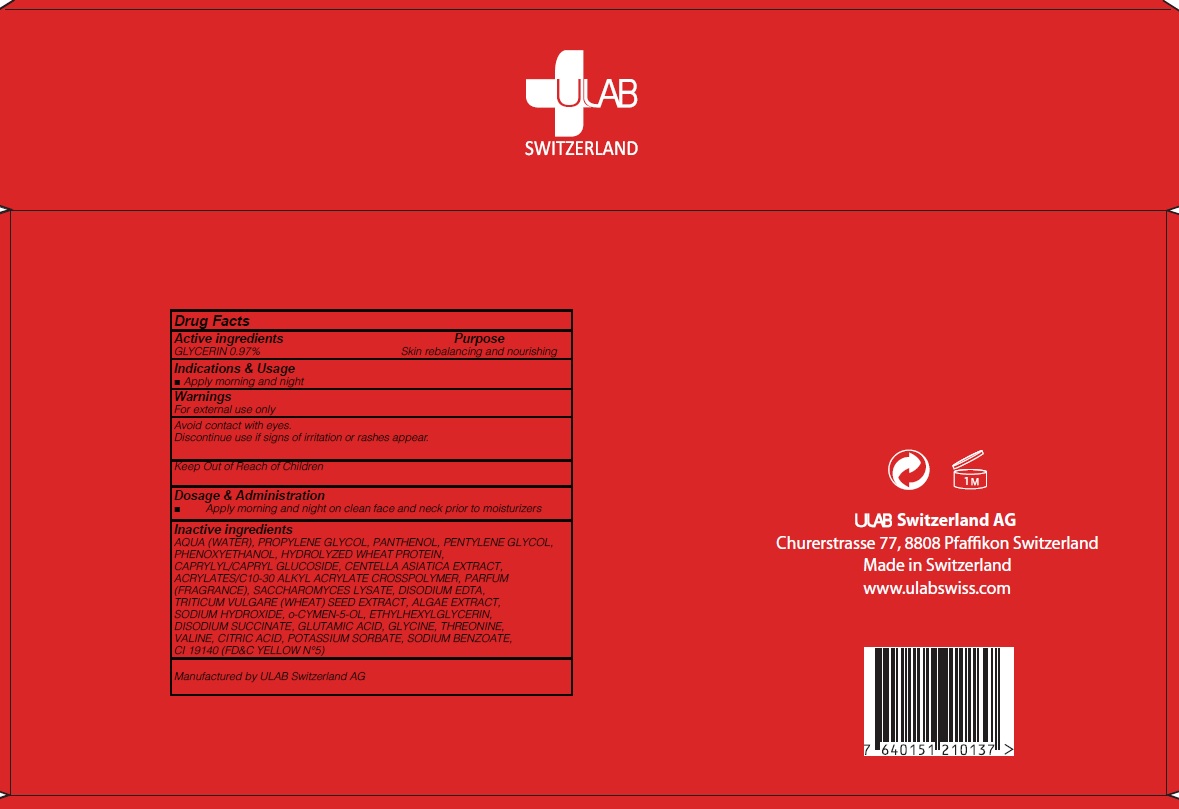 DRUG LABEL: ULTRA REJUVE 7S AMPOULE
NDC: 71276-120 | Form: LIQUID
Manufacturer: ULAB
Category: otc | Type: HUMAN OTC DRUG LABEL
Date: 20170322

ACTIVE INGREDIENTS: GLYCERIN 0.04 g/5 mL
INACTIVE INGREDIENTS: WATER; PROPYLENE GLYCOL

ACTIVE INGREDIENT

Active ingredients: GLYCERIN 0.97%

INACTIVE INGREDIENT

Inactive ingredients: AQUA (WATER), PROPYLENE GLYCOL, PANTHENOL, PENTYLENE GLYCOL, PHENOXYETHANOL, HYDROLYZED WHEAT PROTEIN, CAPRYLYL/CAPRYL GLUCOSIDE, CENTELLA ASIATICA EXTRACT, ACRYLATES/C10-30 ALKYL ACRYLATE CROSSPOLYMER, PARFUM (FRAGRANCE), SACCHAROMYCES LYSATE, DISODIUM EDTA, TRITICUM VULGARE (WHEAT) SEED EXTRACT, ALGAE EXTRACT, SODIUM HYDROXIDE, o-CYMEN-5-OL, ETHYLHEXYLGLYCERIN, DISODIUM SUCCINATE, GLUTAMIC ACID, GLYCINE, THREONINE, VALINE, CITRIC ACID, POTASSIUM SORBATE, SODIUM BENZOATE, CI 19140 (FD&C YELLOW N°5)

PURPOSE

Purpose: Skin rebalancing and nourishing

WARNINGS

Warnings: For external use only Avoid contact with eyes. Discontinue use if signs of irritation or rashes appear.

KEEP OUT OF REACH OF CHILDREN

INDICATIONS & USAGE

Indications & Usage: Apply morning and night

DOSAGE & ADMINISTRATION

Dosage & Administration: Apply morning and night on clean face and neck prior to moisturizers